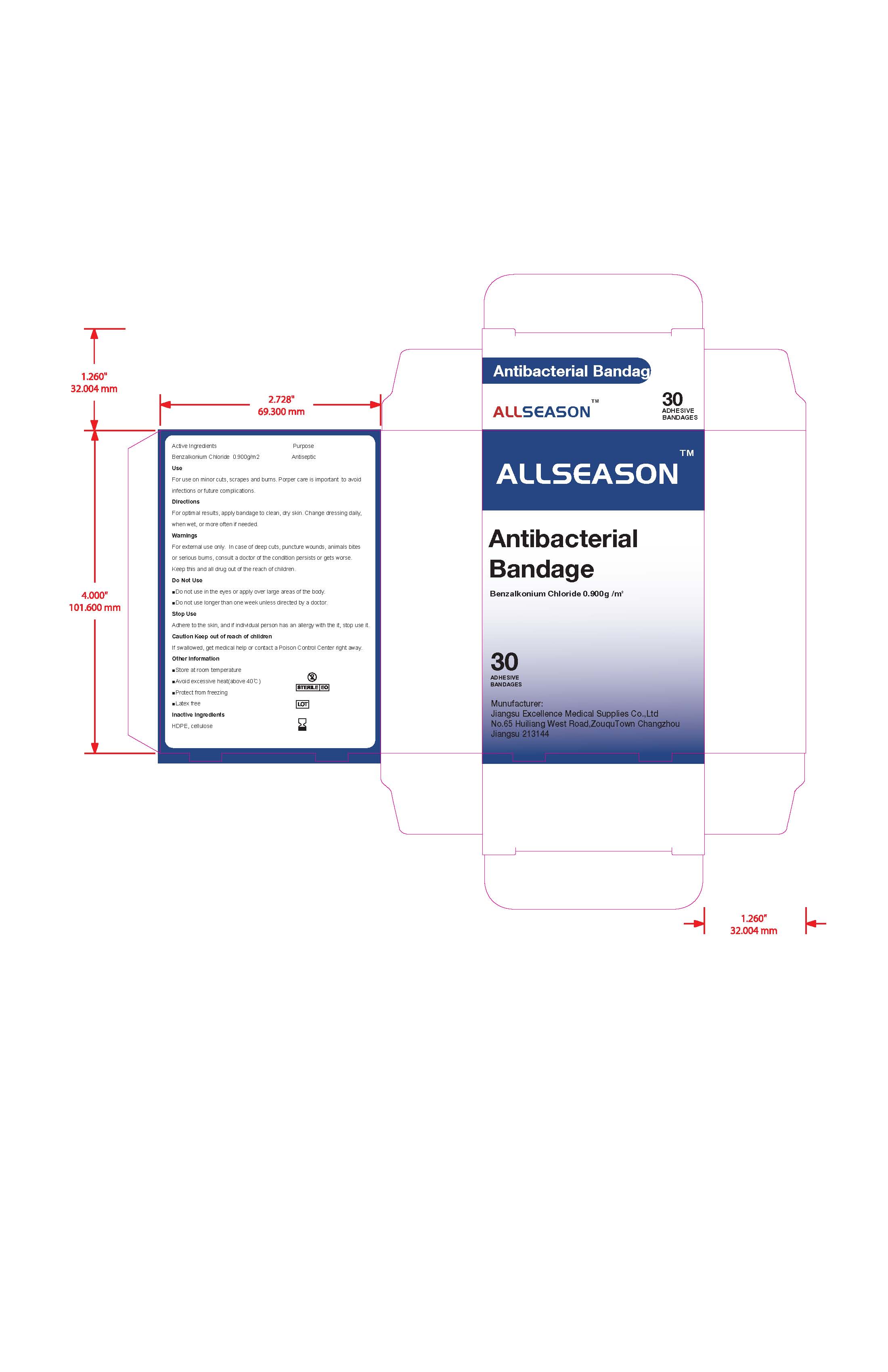 DRUG LABEL: AllSeason Antibacterial Bandage
NDC: 72306-001 | Form: DRESSING
Manufacturer: Excellence Medical Supplies Co., Ltd.
Category: otc | Type: HUMAN OTC DRUG LABEL
Date: 20180606

ACTIVE INGREDIENTS: BENZALKONIUM CHLORIDE 0.28 mg/3.125 cm2
INACTIVE INGREDIENTS: ALPHA CELLULOSE

Drug Fact

Active Ingredient

Benzalkonium Chloride 0.9g /m2

Purpose

Antiseptic

Uses

For use in minor cuts, scrapes and burns.Proper care is important to avoid infections or future complications.

Directions:

For optimal results, apply bandage to clean, dry skin. Change the dressing daily, when wet, ot more often if needed.

Warning:

For external use only. In case of deep cut, puncture wounds, animal bites, or serious burns,consult a doctor if the condition persists or gets worse.

Keep this and all drugs out of reach of children

Do not Use:

Do not use in the eyes or apply over large areas of the body

Do not use longer than one week unless directed by a doctor

Stop Use:

If adhere to the skin, and if individual person has an allergy with it, stop use it.

ASK DOCTOR

Consult a doctor if the condition persists or gets worse.

Keep out of reach of children.

If swallowed, get medical help or contact a poison control center immediately.

Other Information

Store at room temperature

Avoid excessive heat (above 40C)

Protect from freezing

Latex free

Inactive Ingredient:

HDPE, Cellulose